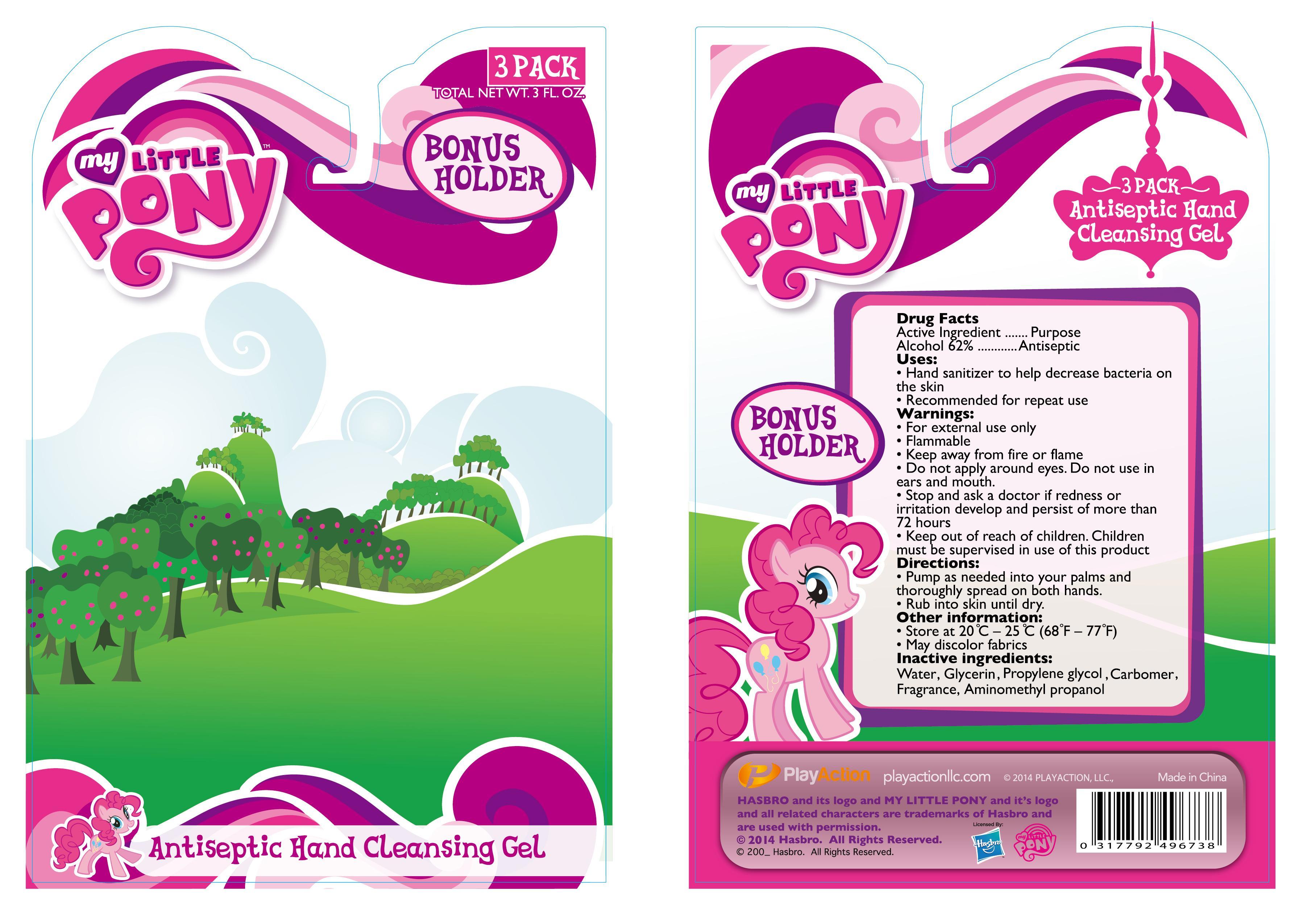 DRUG LABEL: Antiseptic Hand Cleansing Gel
NDC: 69246-001 | Form: GEL
Manufacturer: Playaction LLC
Category: otc | Type: HUMAN OTC DRUG LABEL
Date: 20140924

ACTIVE INGREDIENTS: Alcohol 62 mL/100 mL
INACTIVE INGREDIENTS: WATER; GLYCERIN; PROPYLENE GLYCOL; CARBOMER INTERPOLYMER TYPE A (ALLYL SUCROSE CROSSLINKED); AMINOMETHYLPROPANOL

Active ingredients

Alcohol 62%

Purpose
Antiseptic

Uses:

- Hand sanitizer to help decrease bacteria on the skin.
- Recommended for repeat use.

Warnings: For external use only.

Flammable. Keep away from fire or flame.

Do not apply around eyes.

Do not use in ears or mouth.

Stop use or ask for a doctor if redness or irritation develops and persists for more than 72 hours.

Keep out of reach of children. Children must be supervised in use of this product.

Directions:

- Pump as needed into your palms and thoroughly spread on both hands.
- Rub into skin until dry.

Other information:

- Store at 20 C - 25 C (68 F - 77 F)
- May discolor fabrics

INACTIVE INGREDIENT

INACTIVE INGREDIENTS:Water, Glycerin, Propylene Glycol, Carbomer, Fragrance, Aminomethyl propanol